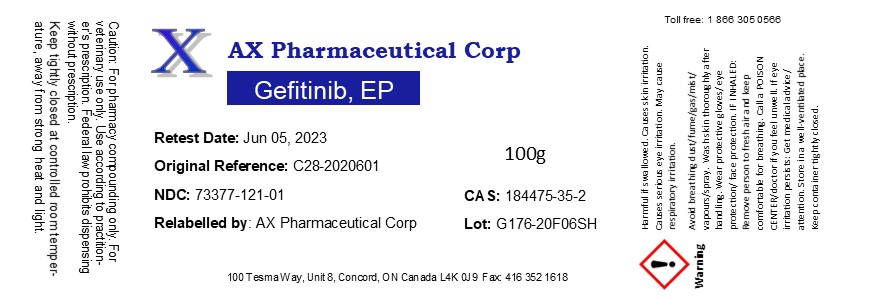 DRUG LABEL: Gefitinib
NDC: 73377-121 | Form: POWDER
Manufacturer: AX Pharmaceutical Corp
Category: other | Type: BULK INGREDIENT
Date: 20210412

ACTIVE INGREDIENTS: GEFITINIB 1 g/1 g

Gefitinib